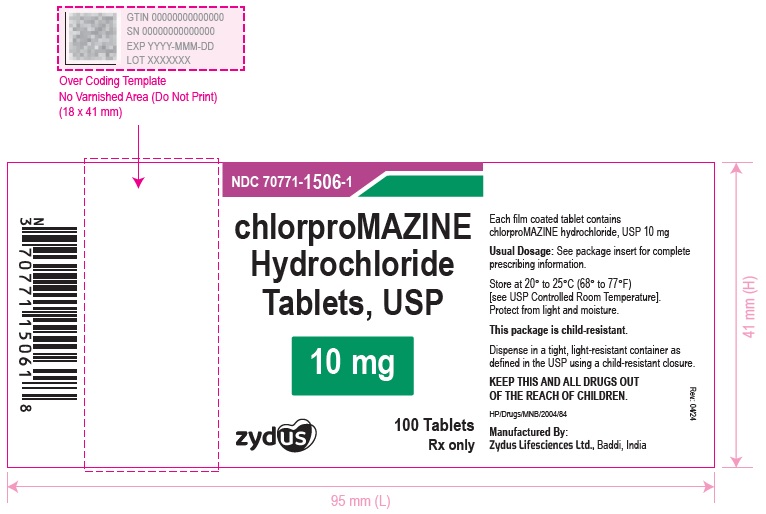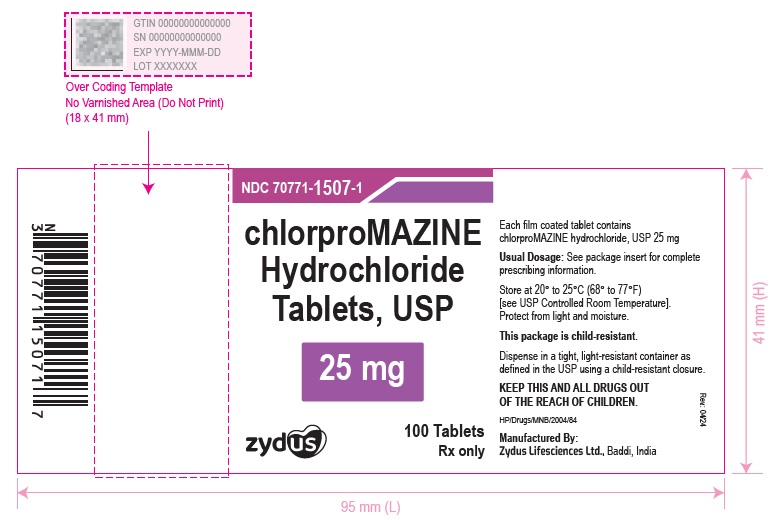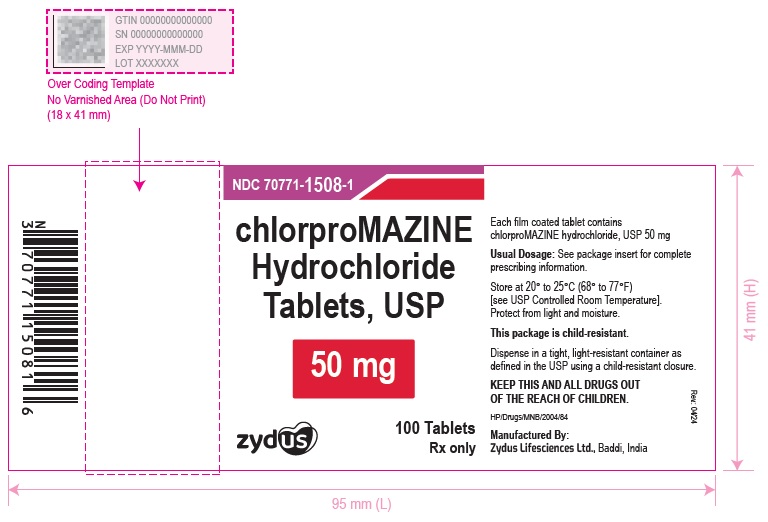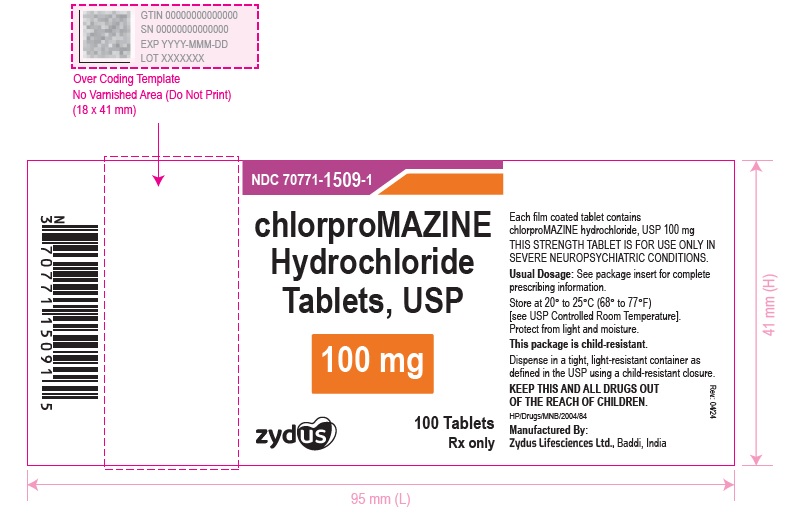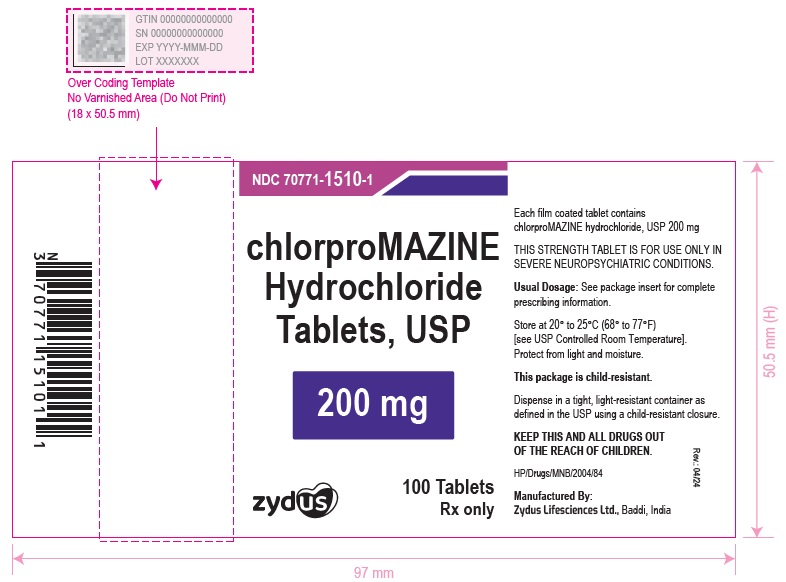 DRUG LABEL: Chlorpromazine hydrochloride
NDC: 70771-1506 | Form: TABLET, FILM COATED
Manufacturer: Zydus Lifesciences Limited
Category: prescription | Type: HUMAN PRESCRIPTION DRUG LABEL
Date: 20240604

ACTIVE INGREDIENTS: CHLORPROMAZINE HYDROCHLORIDE 10 mg/1 1
INACTIVE INGREDIENTS: CALCIUM SULFATE DIHYDRATE; CROSCARMELLOSE SODIUM; FD&C BLUE NO. 2; FD&C YELLOW NO. 6; HYPROMELLOSE 2910 (5 MPA.S); HYPROMELLOSE 2910 (6 MPA.S); LACTOSE MONOHYDRATE; MAGNESIUM STEARATE; MICROCRYSTALLINE CELLULOSE 102; POLYETHYLENE GLYCOL 400; SILICON DIOXIDE; SODIUM STARCH GLYCOLATE TYPE A POTATO; TALC; TITANIUM DIOXIDE

chlorproMAZINE Hydrochloride Tablets, USP
Rx only

PACKAGE LABEL.PRINCIPAL DISPLAY PANEL

NDC 70771-1506-1

chlorproMAZINE Hydrochloride Tablets, USP

10 mg

100 Tablets

Rx only

NDC 70771-1507-1

chlorproMAZINE Hydrochloride Tablets, USP

25 mg

100 Tablets

Rx only

NDC 70771-1508-1

chlorproMAZINE Hydrochloride Tablets, USP

50 mg

100 Tablets

Rx only

NDC 70771-1509-1

chlorproMAZINE Hydrochloride Tablets, USP

100 mg

100 Tablets

Rx only

NDC 70771-1510-1

chlorproMAZINE Hydrochloride Tablets, USP

200 mg

100 Tablets

Rx only